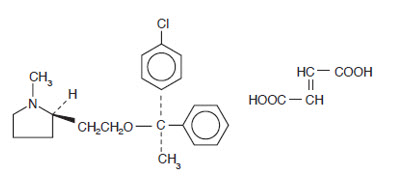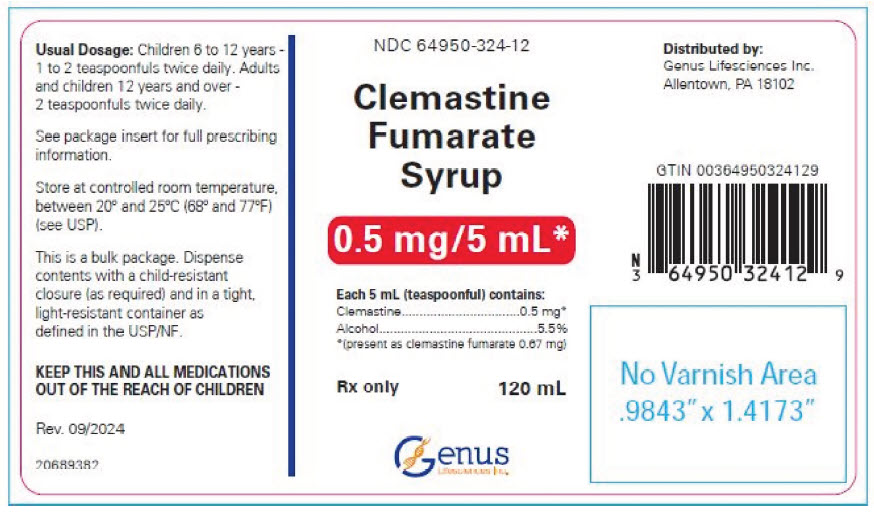 DRUG LABEL: Clemastine Fumarate
NDC: 64950-324 | Form: SYRUP
Manufacturer: Genus Lifesciences
Category: prescription | Type: HUMAN PRESCRIPTION DRUG LABEL
Date: 20241125

ACTIVE INGREDIENTS: Clemastine Fumarate 0.67 mg/5 mL
INACTIVE INGREDIENTS: ALCOHOL; MALEIC ACID; METHYLPARABEN; PROPYLENE GLYCOL; PROPYLPARABEN; SACCHARIN SODIUM; SORBITOL; WATER; SODIUM HYDROXIDE

CLEMASTINE FUMARATE SYRUP, 0.5 mg/5 mL
(present as clemastine fumarate 0.67 mg/5 mL)

Rx only

DESCRIPTION

Each 5 mL (teaspoonful) of Clemastine Fumarate Syrup for oral administration contains clemastine 0.5 mg (present as clemastine fumarate 0.67 mg). Other ingredients: Alcohol 5.5%, Flavors, Maleic Acid, Methylparaben, Propylene Glycol, Propylparaben, Purified Water, Saccharin Sodium, Sodium Hydroxide, and Sorbitol. Clemastine fumarate belongs to the benzhydryl ether group of antihistaminic compounds. The chemical name is (+)-(2R)-2-[2-[[(R)-p-Chloro-α-methyl-α-phenylbenzyl]-oxy]ethyl]-1-methylpyrrolidine fumarate and has the following structural formula:

C21H26ClNO∙C4H4O4

M.W. 459.97

Clemastine fumarate occurs as a colorless to faintly yellow, odorless, crystalline powder. Clemastine Fumarate Syrup has an approximate pH of 6.2.

CLINICAL PHARMACOLOGY

Clemastine fumarate is an antihistamine with anticholinergic (drying) and sedative side effects. Antihistamines competitively antagonize various physiological effects of histamine including increased capillary permeability and dilatation, the formation of edema, the "flare" and "itch" response, and gastrointestinal and respiratory smooth muscle constriction. Within the vascular tree, H1-receptor antagonists inhibit both the vasoconstrictor and vasodilator effects of histamine. Depending on the dose, H1-receptor antagonists can produce CNS stimulation or depression.

Most antihistamines exhibit central and/or peripheral anticholinergic activity. Antihistamines act by competitively blocking H1-receptor sites. Antihistamines do not pharmacologically antagonize or chemically inactivate histamine, nor do they prevent the release of histamine.

Pharmacokinetics

Antihistamines are well-absorbed following oral administration. Chlorpheniramine maleate, clemastine fumarate, and diphenhydramine hydrochloride achieve peak blood levels within 2-5 hours following oral administration. The absorption of antihistamines is often partially delayed by the use of controlled release dosage forms. In these instances, plasma concentrations from identical doses of the immediate and controlled release dosage forms will not be similar. Tissue distribution of the antihistamines in humans has not been established. Antihistamines appear to be metabolized in the liver chiefly via mono- and didemethylation and glucuronide conjugation.

Antihistamine metabolites and small amounts of unchanged drug are excreted in the urine. Small amounts of the drugs may also be excreted in breast milk.

In normal human subjects who received histamine injections over a 24-hour period, the antihistaminic activity of clemastine reached a peak at 5-7 hours, persisted for 10-12 hours and, in some cases, for as long as 24 hours. Pharmacokinetic studies in man utilizing 3H and 14C labeled compound demonstrates that: clemastine is rapidly absorbed from the gastrointestinal tract, peak plasma concentrations are attained in 2-4 hours, and urinary excretion is the major mode of elimination.

INDICATIONS AND USAGE

Clemastine Fumarate Syrup is indicated for the relief of symptoms associated with allergic rhinitis such as sneezing, rhinorrhea, pruritus and lacrimation. Clemastine Fumarate Syrup is indicated for use in pediatric populations (age 6 years through 12) and adults (see DOSAGE AND ADMINISTRATION).

It should be noted that clemastine is indicated for the relief of mild uncomplicated allergic skin manifestations of urticaria and angioedema at the 2 mg dosage level only.

CONTRAINDICATIONS

Antihistamines are contraindicated in patients hypersensitive to the drug or to other antihistamines of similar chemical structure (see PRECAUTIONS- Drug Interactions).

Antihistamines should not be used in newborn or premature infants. Because of the higher risk of antihistamines for infants generally and for newborns and prematures in particular, antihistamine therapy is contraindicated in nursing mothers (see PRECAUTIONS-Nursing Mothers).

WARNINGS

Antihistamines should be used with considerable caution in patients with: narrow angle glaucoma, stenosing peptic ulcer, pyloroduodenal obstruction, symptomatic prostatic hypertrophy, and bladder neck obstruction.

Use with CNS Depressants

Clemastine has additive effects with alcohol and other CNS depressants (hypnotics, sedatives, tranquilizers, etc.).

Use in Activities Requiring Mental Alertness

Patients should be warned about engaging in activities requiring mental alertness such as driving a car or operating appliances, machinery, etc.

Use in the Elderly (approximately 60 years or older)

Antihistamines are more likely to cause dizziness, sedation, and hypotension in elderly patients.

PRECAUTIONS

General

Clemastine fumarate should be used with caution in patients with:

history of bronchial asthma, increased intraocular pressure, hyperthyroidism, cardiovascular disease, and hypertension.

Information for Patients

Patients taking antihistamines should receive the following information and instructions:

1. Antihistamines are prescribed to reduce allergic symptoms.
2. Patients should be questioned regarding a history of glaucoma, peptic ulcer, urinary retention, or pregnancy before starting antihistamine therapy.
3. Patients should be told not to take alcohol, sleeping pills, sedatives, or tranquilizers while taking antihistamines.
4. Antihistamines may cause drowsiness, dizziness, dry mouth, blurred vision, weakness, nausea, headache, or nervousness in some patients.
5. Patients should avoid driving a car or working with hazardous machinery until they assess the effects of this medicine.
6. Patients should be told to store this medicine in a tightly closed container in a dry, cool place away from heat or direct sunlight and out of the reach of children.

Drug Interactions

Additive CNS depression may occur when antihistamines are administered concomitantly with other CNS depressants including barbiturates, tranquilizers, and alcohol. Patients receiving antihistamines should be advised against the concurrent use of other CNS depressant drugs. Monoamine oxidase (MAO) inhibitors prolong and intensify the anticholinergic effects of antihistamines.

Carcinogenesis, Mutagenesis, Impairment of Fertility

Carcinogenesis and Mutagenesis

In a 2-year oral study in the rat at a dose of 84 mg/kg (about 500 times the adult human dose) and an 85-week oral study in the mouse at 206 mg/kg (about 1300 times the adult human dose), clemastine fumarate showed no evidence of carcinogenesis. No mutagenic studies have been conducted with clemastine fumarate.

Impairment of Fertility

Oral doses of clemastine fumarate in the rat produced a decrease in mating ability of the male at 312 times the adult human dose. This effect was not found at 156 times the adult human dose.

Pregnancy

Teratogenic Effects

Pregnancy Category B

Oral reproduction studies performed with clemastine fumarate in rats and rabbits at doses up to 312 and 188 times the adult human doses respectively, have revealed no evidence of teratogenic effects.

There are no adequate and well-controlled studies of clemastine fumarate in pregnant women. Because animal reproduction studies are not always predictive of human response, this drug should be used in pregnancy only if clearly needed.

Nursing Mothers

Although quantitative determinations of antihistaminic drugs in breast milk have not been reported, qualitative tests have documented the excretion of diphenhydramine, pyrilamine, and tripelennamine in human milk.

Because of the potential for adverse reactions in nursing infants from antihistamines, a decision should be made whether to discontinue nursing or to discontinue the drug.

Pediatric Use

The safety and efficacy of Clemastine Fumarate Syrup has been confirmed in the pediatric population (age 6 years through 12). Safety and dose tolerance studies have confirmed pediatric patients 6 through 11 years tolerated dosage ranges of 0.75 to 2.25 mg clemastine. In pediatric patients particularly, antihistamines in overdosage may produce hallucinations, convulsions and death. Symptoms of antihistamine toxicity in pediatric patients may include fixed dilated pupils, flushed face, dry mouth, fever, excitation, hallucinations, ataxia, incoordination, athetosis, tonic- lonic convulsions, and postictal depression (see OVERDOSAGE).

ADVERSE REACTIONS

The most frequent adverse reactions are italicized:

Nervous System

Sedation, sleepiness, dizziness, disturbed coordination, fatigue, confusion, restlessness, excitation, nervousness, tremor, irritability, insomnia, euphoria, paresthesia, blurred vision, diplopia, vertigo, tinnitus, acute labyrinthitis, hysteria, neuritis, convulsions.

Gastrointestinal System

Epigastric distress, anorexia, nausea, vomiting, diarrhea, constipation.

Respiratory System

Thickening of bronchial secretions, tightness of chest and wheezing, nasal stuffiness.

Cardiovascular System

Hypotension, headache, palpitations, tachycardia, extrasystoles.

Hematologic System

Hemolytic anemia, thrombocytopenia, agranulocytosis.

Genitourinary System

Urinary frequency, difficult urination, urinary retention, early menses.

General

Urticaria, drug rash, anaphylactic shock, photosensitivity, excessive perspiration, chills, dryness of mouth, nose and throat.

To report SUSPECTED ADVERSE REACTIONS, contact Allucent at 1-866-511-6754 or FDA at 1-800-FDA-1088 or www.fda.gov/medwatch.

OVERDOSAGE

Antihistamine overdosage reactions may vary from central nervous system depression to stimulation. In children, stimulation predominates initially in a syndrome which may include excitement, hallucinations, ataxia, incoordination, muscle twitching, athetosis, hyperthermia,

cyanosis convulsions, tremors, and hyperreflexia followed by postictal depression and cardio-respiratory arrest. Convulsions in children may be preceded by mild depression. Dry mouth, fixed dilated pupils, flushing of the face, and fever are common. In adults, CNS depression, ranging from drowsiness to coma, is more common. The convulsant dose of antihistamines lies near the lethal dose. Convulsions indicate a poor prognosis.

In both children and adults, coma and cardiovascular collapse may occur.

Deaths are reported especially in infants and children.

There is no specific therapy for acute overdosage with antihistamines. The latent period from ingestion to appearance of toxic effects is characteristically short (1/2-2 hours). General symptomatic and supportive measures should be instituted promptly and maintained for as long as necessary.

Since overdoses of other classes of drugs (i.e. tricyclic antidepressants) may also present anticholinergic symptomatology, appropriate toxicological analysis should be performed as soon as possible to identify the causative agent.

In the conscious patient, vomiting should be induced even though it may have occurred spontaneously. If vomiting cannot be induced, gastric lavage is indicated. Adequate precautions must be taken to protect against aspiration, especially in infants and children. Charcoal slurry or

other suitable agents should be instilled into the stomach after vomiting or lavage. Saline cathartics or milk of magnesia may be of additional benefit.

In the unconscious patient, the airway should be secured with a cuffed endotracheal tube before attempting to evacuate the gastric contents. Intensive supportive and nursing care is indicated, as for any comatose patient.

If breathing is significantly impaired, maintenance of an adequate airway and mechanical support of respiration is the most effective means of providing adequate oxygenation.

Hypotension is an early sign of impending cardiovascular collapse and should be treated vigorously. Although general supportive measures are important, specific treatment with intravenous infusion of a vasopressor titrated to maintain adequate blood pressure may be necessary.

Do not use with CNS stimulants.

Convulsions should be controlled by careful administration of diazepam or a short-acting barbiturate, repeated as necessary. Physostigmine may also be considered for use in controlling centrally mediated convulsions.

Ice packs and cooling sponge baths, not alcohol, can aid in reducing the fever commonly seen in children. A more detailed review of antihistamine toxicology and overdose management is available in Gosselin, R.E., et. al., "Clinical Toxicology of Commercial Products."

DOSAGE AND ADMINISTRATION

DOSAGE SHOULD BE INDIVIDUALIZED ACCORDING TO THE NEEDS AND RESPONSE OF THE PATIENT.

Pediatric

Children aged 6 to 12 years

For Symptoms of Allergic Rhinitis

The starting dose is 1 teaspoonful (0.5 mg clemastine) twice daily. Since single doses of up to 2.25 mg clemastine were well tolerated by this age group, dosage may be increased as required, but not to exceed 6 teaspoonfuls daily (3 mg clemastine).

For Urticaria and Angioedema

The starting dose is 2 teaspoonfuls (1 mg clemastine) twice daily, not to exceed 6 teaspoonfuls daily (3 mg clemastine).

Adults and Children 12 Years and Over

For Symptoms of Allergic Rhinitis

The starting dose is 2 teaspoonfuls (1 mg clemastine) twice daily. Dosage may be increased as required, but not to exceed 12 teaspoonfuls daily (6 mg clemastine).

For Urticaria and Angioedema

The starting dose is 4 teaspoonfuls (2 mg clemastine) twice daily, not to exceed 12 teaspoonfuls daily (6 mg clemastine).

HOW SUPPLIED

Clemastine Fumarate Syrup: clemastine 0.5 mg/5 mL (present as clemastine fumarate 0.67 mg/5 mL). A clear, colorless liquid with a citrus flavor (passion fruit), in 120 mL bottle.

120 mL bottle (NDC 64950-324-12)

STORAGE AND HANDLING

Store at controlled room temperature, between 20° and 25°C (68° and 77°F) (see USP).

Distributed By:

Genus Lifesciences Inc.
Allentown, PA 18102
Rev. 09/24

PRINCIPAL DISPLAY PANEL - 120 mL Bottle Label

NDC 64950-324-12

Clemastine
Fumarate
Syrup

0.5 mg/5 mL*

Each 5 mL (teaspoonful) contains:

Clemastine 0.5 mg*

Alcohol 5.5%

*(present as clemastine fumarate 0.67 mg)

Rx only
120 mL

Genus
Lifesciences Inc.